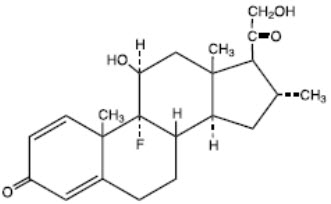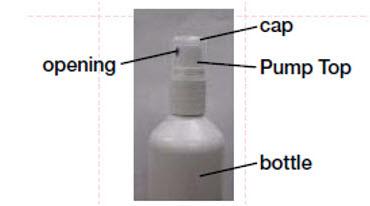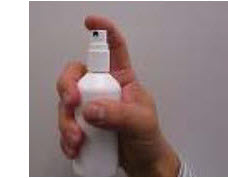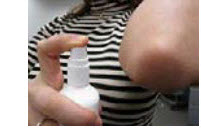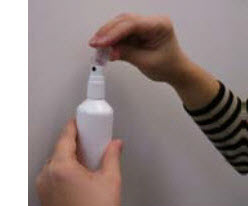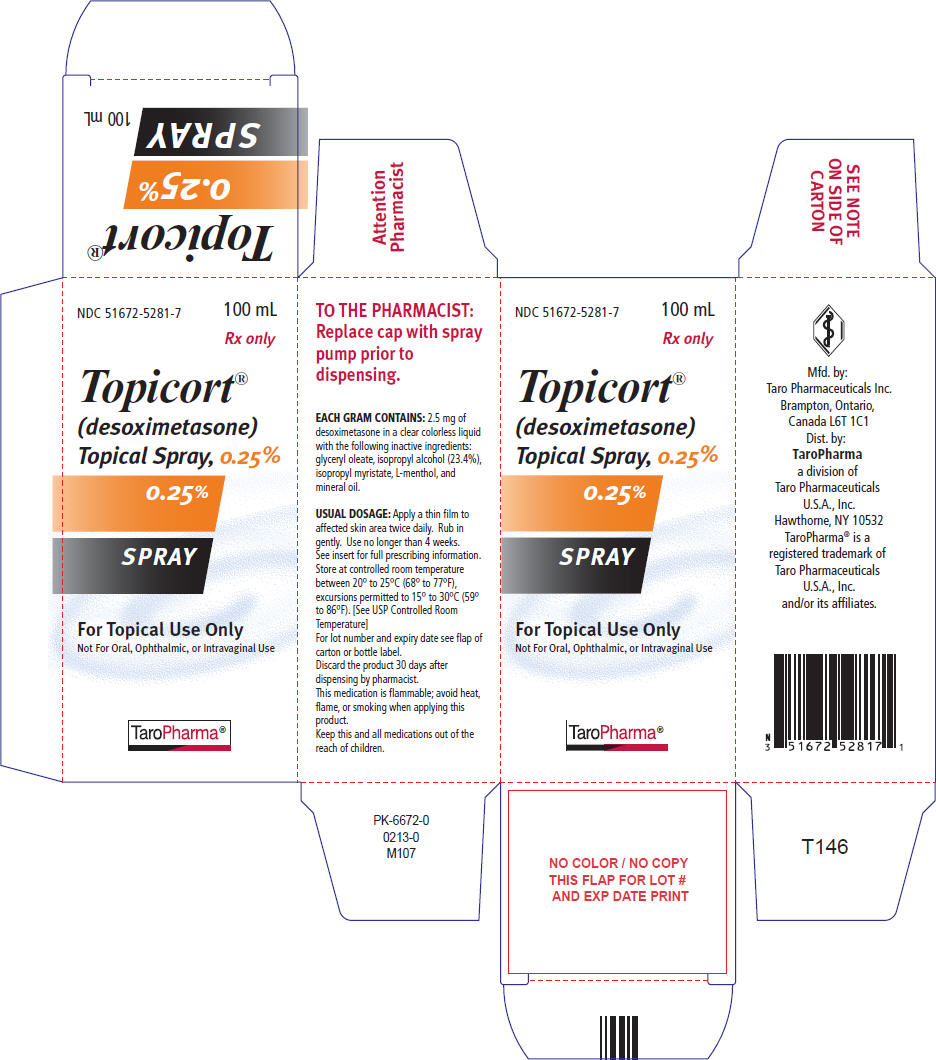 DRUG LABEL: Topicort
NDC: 51672-5281 | Form: SPRAY
Manufacturer: Sun Pharmaceutical Industries, Inc.
Category: prescription | Type: HUMAN PRESCRIPTION DRUG LABEL
Date: 20250702

ACTIVE INGREDIENTS: DESOXIMETASONE 2.5 mg/1 mL
INACTIVE INGREDIENTS: GLYCERYL OLEATE; ISOPROPYL ALCOHOL; ISOPROPYL MYRISTATE; LEVOMENTHOL; MINERAL OIL

HIGHLIGHTS OF PRESCRIBING INFORMATION

These highlights do not include all the information needed to use TOPICORT®topical spray safely and effectively. See full prescribing information for TOPICORT®topical spray.
TOPICORT®(desoximetasone) topical spray
Initial U.S. Approval: 1977

1 INDICATIONS AND USAGE

Topicort®Topical Spray is a corticosteroid indicated for the treatment of plaque psoriasis in patients 18 years of age or older (1).

2 DOSAGE AND ADMINISTRATION

- Apply a thin film to the affected skin areas twice daily. Rub in gently. (2)
- Discontinue treatment when control is achieved. (2)
- Treatment beyond 4 weeks is not recommended. (2)
- Do not use if atrophy is present at the treatment site. (2)
- Do not use with occlusive dressings, unless directed by the physician. (2)
- Avoid use on the face, axilla or groin. (2)
- Not for oral, ophthalmic, or intravaginal use. (2)

3 DOSAGE FORMS AND STRENGTHS

Spray, 0.25% w/w (3)

4 CONTRAINDICATIONS

None (4)

5 WARNINGS AND PRECAUTIONS

- Effect on Endocrine System:Topicort®Topical Spray can produce reversible HPA axis suppression with the potential for glucocorticosteroid insufficiency during or after treatment. (5.1)
  - Cushing's syndrome, hyperglycemia, and unmasking of latent diabetes mellitus can result from systemic absorption of topical corticosteroids. (5.1)
  - Because of the potential for systemic absorption, use of topical corticosteroids may require that patients be periodically evaluated for HPA axis suppression. (5.1)
  - Modify use if HPA axis suppression develops. (5.1)
  - High potency corticosteroids, large treatment surface areas, prolonged use, use of occlusive dressings, altered skin barrier, liver failure and young age may predispose patients to HPA axis suppression. (5.1)
  - Pediatric patients may be more susceptible to systemic toxicity when treated with topical corticosteroids. Safety and effectiveness have not been established in pediatric patients and use in pediatric patients is not recommended. (5.1, 8.4)
- Ophthalmic Adverse Reactions:Topical corticosteroid products may increase the risk of cataracts and glaucoma. If visual symptoms occur, consider referral to an ophthalmologist. (5.3).
- Flammability:Topicort Topical Spray is flammable; keep away from heat or flame. (5.6)

6 ADVERSE REACTIONS

The most common adverse reactions (≥ 1%) are application site dryness, application site irritation and application site pruritus. (6.1)

To report SUSPECTED ADVERSE REACTIONS, contact Taro Pharmaceuticals U.S.A., Inc. at 1-866-923-4914 or FDA at 1-800-FDA-1088 or www.fda.gov/medwatch.

FULL PRESCRIBING INFORMATION

1 INDICATIONS AND USAGE

Topicort®Topical Spray is a corticosteroid indicated for the treatment of plaque psoriasis in patients 18 years of age or older.

2 DOSAGE AND ADMINISTRATION

Apply Topicort Topical Spray as a thin film to the affected skin areas twice daily. Rub in gently.

Do not bandage or otherwise cover or wrap the treated skin unless directed by the physician.

Discontinue treatment when control is achieved.

Treatment beyond 4 weeks is not recommended.

Do not use if atrophy is present at the treatment site.

Avoid use on the face, axilla or groin.

Topicort Topical Spray is for external use only. It is not for oral, ophthalmic, or intravaginal use.

3 DOSAGE FORMS AND STRENGTHS

Topical Spray, 0.25%. Each gram of Topicort Topical Spray contains 2.5 mg of desoximetasone in a clear, colorless liquid.

4 CONTRAINDICATIONS

None

5 WARNINGS AND PRECAUTIONS

5.1 Effect on Endocrine System

Topicort Topical Spray is a topical corticosteroid that has been shown to suppress the hypothalamic-pituitary-adrenal (HPA) axis.

Systemic absorption of topical corticosteroids can produce reversible HPA axis suppression with the potential for glucocorticosteroid insufficiency. This may occur during treatment or upon withdrawal of the topical corticosteroid.

In a study including 21 evaluable subjects 18 years of age or older with moderate to severe plaque psoriasis, adrenal suppression was identified in 1 out of 12 subjects having involvement of 10 to15% of body surface area (BSA) and 2 out of 9 subjects having involvement of >15% of BSA after treatment with Topicort Topical Spray twice a day for 28 days [see Clinical Pharmacology (12.2)] .

Because of the potential for systemic absorption, use of topical corticosteroids may require that patients be periodically evaluated for HPA axis suppression. Factors that predispose a patient using a topical corticosteroid to HPA axis suppression include the use of high potency steroids, larger treatment surface areas, prolonged use, use of occlusive dressings, altered skin barrier, liver failure and young age.

An ACTH stimulation test may be helpful in evaluating patients for HPA axis suppression.

If HPA axis suppression is documented, an attempt should be made to gradually withdraw the drug, to reduce the frequency of application, or to substitute a less potent steroid. Manifestations of adrenal insufficiency may require supplemental systemic corticosteroids. Recovery of HPA axis function is generally prompt and complete upon discontinuation of topical corticosteroids.

Cushing's syndrome, hyperglycemia, and unmasking of latent diabetes mellitus can also result from systemic absorption of topical corticosteroids.

Use of more than one corticosteroid-containing product at the same time may increase the total systemic corticosteroid exposure.

Pediatric patients may be more susceptible to systemic toxicity from use of topical corticosteroids. Use in patients under 18 years of age is not recommended due to numerically high rates of HPA axis suppression (the safety and effectiveness of Topicort Topical Spray have not been established in pediatric patients) [see Use in Specific Populations (8.4)and Clinical Pharmacology (12.2)] .

5.2 Local Adverse Reactions with Topical Corticosteroids

Local adverse reactions may be more likely to occur with occlusive use, prolonged use or use of higher potency corticosteroids. Reactions may include atrophy, striae, telangiectasias, burning, itching, irritation, dryness, folliculitis, acneiform eruptions, hypopigmentation, perioral dermatitis, allergic contact dermatitis, secondary infection, and miliaria. Some local adverse reactions may be irreversible.

5.3 Ophthalmic Adverse Reactions

Use of topical corticosteroids, including Topicort Topical Spray, may increase the risk of posterior subcapsular cataracts and glaucoma. Cataracts and glaucoma have been reported with the postmarketing use of topical corticosteroid products [see Adverse Reactions (6.2)] . Avoid contact of Topicort Topical Spray with eyes. Topicort Topical Spray may cause eye irritation. Advise patients to report any visual symptoms and consider referral to an ophthalmologist for evaluation .

5.4 Allergic Contact Dermatitis with Topical Corticosteroids

Allergic contact dermatitis to any component of topical corticosteroids is usually diagnosed by a failure to heal rather than a clinical exacerbation. Clinical diagnosis of allergic contact dermatitis can be confirmed by patch testing.

5.5 Concomitant Skin Infections

Concomitant skin infections should be treated with an appropriate antimicrobial agent.

If the infection persists, Topicort Topical Spray should be discontinued until the infection has been adequately treated.

5.6 Flammability

Topicort Topical Spray is flammable; keep away from heat or flame.

6 ADVERSE REACTIONS

6.1 Clinical Trials Experience

Because clinical trials are conducted under widely varying conditions, adverse reaction rates observed in the clinical trials of a drug cannot be directly compared to rates in the clinical trials of another drug and may not reflect the rates observed in practice.

In randomized, multicenter, prospective vehicle-controlled clinical trials, subjects with moderate to severe plaque psoriasis of the body applied Topicort Topical Spray or vehicle spray twice daily for 4 weeks. A total of 149 subjects applied Topicort Topical Spray.

Adverse reactions that occurred in ≥ 1% of subjects treated with Topicort Topical Spray are presented in Table 1.

Table 1. Number (%) of Subjects with Adverse Reactions Occurring in ≥ 1%
 | Topicort Topical Spray, 0.25% b.i.d. (N = 149) | Vehicle spray b.i.d. (N = 135)
Number of Subjects with Adverse Reactions | 13 (8.7%) | 18 (13.3%)
Application site dryness | 4 (2.7%) | 7 (5.2%)
Application site irritation | 4 (2.7%) | 5 (3.7%)
Application site pruritus | 3 (2.0%) | 5 (3.7%)

Another less common adverse reaction (<1% but >0.1%) was folliculitis.

6.2 Postmarketing Experience

Because adverse reactions are reported voluntarily from a population of uncertain size, it is not always possible to reliably estimate their frequency or establish a causal relationship to drug exposure.

Postmarketing reports for local adverse reactions to topical corticosteroids included atrophy, striae, telangiectasias, itching, dryness, hypopigmentation, perioral dermatitis, secondary infection, and miliaria.

Ophthalmic adverse reactions of cataracts, glaucoma, and increased intraocular pressure have been reported during use of topical corticosteroids.

8 USE IN SPECIFIC POPULATIONS

8.1 Pregnancy

Risk Summary

There are no available data on desoximetasone use in pregnant women to evaluate for a drug-associated risk of major birth defects, miscarriage or adverse maternal or fetal outcomes. Observational studies suggest maternal use of high to super-high potency topical steroids, including Topicort Topical Spray, may be associated with an increased risk of low birthweight infants (see Data). Advise pregnant woman that Topicort Topical Spray may increase the potential risk of low birth weight infants and to use Topicort Topical Spray on the smallest area of skin and for the shortest duration possible.

Desoximetasone has been shown to cause malformations and be embryotoxic in mice, rats, and rabbits when given by subcutaneous or dermal routes of administration at doses 3 to 30 times the human dose of Topicort Topical Spray based on a body surface area comparison.

The background risk of major birth defects and miscarriage for the indicated population is unknown. All pregnancies have a background risk of birth defect, loss, or other adverse outcomes. In the U.S. general population, the estimated background risk of major birth defects and miscarriage in clinically recognized pregnancies is 2 to 4% and 15 to 20%, respectively.

Data

Human Data

Available observational studies in pregnant women did not identify a drug-associated risk of major birth defects, preterm delivery, or fetal mortality with the use of topical corticosteroids of any potency. However, when the dispensed amount of high to super-high potency topical corticosteroids exceeded 300g during the entire pregnancy, maternal use was associated with an increased risk of low birth weight in infants.

8.2 Lactation

Risk Summary

There is no information on the presence of topically administered desoximetasone in human milk, the effects on the breastfed infant, or the effects on milk production. It is not known whether topical administration of corticosteroids could result in sufficient systemic absorption to produce detectable quantities in breast milk. The developmental and health benefits of breastfeeding should be considered along with the mother's clinical need for Topicort Topical Spray and any potential adverse effects on the breastfed infant from Topicort Topical Spray or from the underlying maternal condition.

Clinical Considerations

To minimize potential exposure to the breastfed infant via breast milk, use Topicort Topical Spray on the smallest area of skin and for the shortest duration possible while breastfeeding. Advise breastfeeding women not to apply Topicort Topical Spray directly to the nipple and areola to avoid direct infant exposure [see Warnings and Precautions (5.1)and Use in Specific Populations (8.4)].

8.4 Pediatric Use

The safety and effectiveness of Topicort Topical Spray have not been established in pediatric patients for the treatment of plaque psoriasis. Topicort Topical Spray is not recommended for use in patients less than 18 years of age due to the high incidence of HPA axis suppression observed [see Warnings and Precautions (5.1)].

Hypothalamic-Pituitary Adrenal (HPA) Axis Suppression

The HPA axis suppression potential of Topicort Topical Spray was assessed in an open-label, sequential cohort, safety trial in 129 subjects 2 years to less than 18 years of age with moderate to severe plaque psoriasis defined as a Physician Global Assessment (PGA) score of ≥3 with involvement of at least 10% of their body surface area (excluding the face and scalp). In total, 100 pediatric subjects were evaluated for HPA axis function via cosyntropin stimulation testing at baseline and following 4 weeks of twice daily application of Topicort Topical Spray. Overall, 36% of pediatric subjects 2 years to less than 18 years of age demonstrated HPA axis suppression defined as a serum cortisol level ≤ 18 mcg/dL 30-minutes post cosyntropin stimulation. The proportion of subjects demonstrating HPA axis suppression was 35.0% in Cohort 1 (12 years to less than 18 years of age) and 43.3% in Cohort 2 (6 years to less than 12 years of age). Trial enrollment in the youngest cohort (2 years to less than 6 years of age) was discontinued early due to high incidence of HPA axis suppression observed in the two oldest cohorts (6 years to less than 18 years of age) [see Clinical Pharmacology (12.2)] .

Because of a higher ratio of skin surface area to body mass, pediatric patients are at a greater risk than adults of HPA axis suppression and Cushing's syndrome when they are treated with topical corticosteroids. They are therefore at greater risk of adrenal insufficiency during and/or after withdrawal of treatment. Adverse reactions including striae have been reported with inappropriate use of topical corticosteroids in infants and children.

HPA axis suppression, Cushing's syndrome, linear growth retardation, delayed weight gain, and intracranial hypertension have been reported in children receiving topical corticosteroids. Manifestations of adrenal suppression in children include low plasma cortisol levels and absence of response to ACTH stimulation. Manifestations of intracranial hypertension include bulging fontanelles, headaches, and bilateral papilledema.

8.5 Geriatric Use

Clinical studies of Topicort Topical Spray did not include sufficient numbers of subjects aged 65 years and over to determine whether they respond differently from younger subjects. Other reported clinical experience has not identified differences in responses between the elderly and younger patients. In general, dose selection for an elderly patient should be cautious, usually starting at the low end of the dosing range, reflecting the greater frequency of decreased hepatic, renal, or cardiac function, and of concomitant disease or other drug therapy.

10 OVERDOSAGE

Topicort Topical Spray can be absorbed in sufficient amounts to produce systemic effects [see Warnings and Precautions (5.1)] .

11 DESCRIPTION

Topicort®(desoximetasone) Topical Spray, 0.25% for dermatologic use contains desoximetasone as the active ingredient.

Desoximetasone is a corticosteroid with the chemical name of pregna-1, 4-diene-3, 20-dione, 9-fluoro-11, 21-dihydroxy-16-methyl-, (11β,16α)-.

Desoximetasone has the molecular formula of C22H29FO4and a molecular weight of 376.47. The CAS Registry Number is 382-67-2.

The structural formula is:

Each gram of Topicort®Topical Spray contains 2.5 mg of desoximetasone in a clear, colorless liquid with the following inactive ingredients: glyceryl oleate, isopropyl alcohol (23.4%), isopropyl myristate, L-menthol, and mineral oil. Topicort®Topical Spray is co-packaged with a manual spray pump for installation by the pharmacist prior to dispensing to patients.

12 CLINICAL PHARMACOLOGY

12.1 Mechanism of Action

Corticosteroids play a role in cellular signaling, immune function, inflammation and protein regulation; however, the precise mechanism of action in psoriasis is unknown.

12.2 Pharmacodynamics

Vasoconstrictor Assay

Vasoconstrictor studies performed with Topicort Topical Spray in healthy subjects indicate that it is in the high to super-high range of potency as compared with other topical corticosteroids.

Hypothalamic-Pituitary Adrenal (HPA) Axis Suppression

The potential for hypothalamic-pituitary-adrenal (HPA) axis suppression was evaluated in two trials. Topicort Topical Spray was applied twice a day for 28 days and HPA axis suppression was defined as serum cortisol level ≤18 mcg/dL 30-min post cosyntropin stimulation.

In the first trial, out of 24 adult subjects with moderate to severe plaque psoriasis, 21 subjects had evaluable serum cortisol levels. The proportion of subjects demonstrating HPA axis suppression was 8.3% (1 out of 12) in subjects having psoriasis involvement of 10-15% of body surface area (BSA), and 22.2% (2 out of 9) in subjects having psoriasis involvement of > 15% of their BSA. In the 2 subjects with available follow-up values, suppression reversed 28 days after the end of treatment.

In another trial, the HPA axis suppression was evaluated in 106 pediatric subjects with moderate to severe plaque psoriasis. One hundred subjects had evaluable serum cortisol levels. The proportion of subjects demonstrating HPA axis suppression was 35.0% (21 out of 60) in Cohort 1 (12 years to less than 18 years of age, with a mean baseline BSA involvement of 16%), and 43.3% (13 out of 30) in Cohort 2 (6 years to less than 12 years of age, with a mean baseline BSA involvement of 19%). Trial enrollment in the youngest cohort (2 years to less than 6 years of age) was discontinued early due to high incidence of HPA axis suppression observed in the two oldest cohorts (6 years to less than 18 years of age). The overall HPA axis suppression rate was 36% in pediatric subjects 2 years to less than 18 years of age. Due to high incidence of HPA axis suppression observed from this trial, Topicort Topical Spray is not recommended for use in pediatric patients less than 18 years of age [see Use in Specific Populations (8.4)].

12.3 Pharmacokinetics

The extent of percutaneous absorption of topical corticosteroids is determined by many factors including the vehicle, the integrity of the epidermal barrier, and the use of occlusive dressings.

Topical corticosteroids can be absorbed from normal intact skin. Inflammation and/or other disease processes in the skin increase percutaneous absorption. Occlusive dressings substantially increase the percutaneous absorption of topical corticosteroids. Once absorbed through the skin, topical corticosteroids are handled through pharmacokinetic pathways similar to systemically administered corticosteroids. Corticosteroids are bound to plasma proteins in varying degrees. Corticosteroids are metabolized primarily in the liver and are then excreted by the kidneys. Some of the topical corticosteroids and their metabolites are also excreted into the bile.

Plasma concentrations of desoximetasone were measured at two single random time points in the HPA axis suppression trial in 24 adult subjects with psoriasis [see Clinical Pharmacology (12.2)] . The mean (% Coefficient of Variation) concentration of desoximetasone was 449 pg/mL (86%) at Day 14 and 678 pg/mL (135%) at Day 28. The concentration time profile following application of Topicort Topical Spray is not known.

In the pediatric HPA axis suppression trial, plasma concentrations of desoximetasone were measured in a subset of subjects in Cohorts 1 and 2 [see Clinical Pharmacology (12.2)] . High inter subject variability in plasma concentrations was observed in both cohorts. The mean (% Coefficient of Variation) maximum concentration on Day 29 was 1881 pg/mL (127%) in Cohort 1 (n=11) and 1116 pg/mL (94%) in Cohort 2 (n=8).

13 NONCLINICAL TOXICOLOGY

13.1 Carcinogenesis, Mutagenesis, Impairment of Fertility

Long-term animal studies have not been performed to evaluate the carcinogenic potential of Topicort Topical Spray.

In a 13-week repeat-dose toxicity study in rats, topical administration of desoximetasone spray at concentrations of 0.001, 0.005 and 0.02% BID (which corresponds to dose levels of 0.01, 0.05, or 0.2 mg/kg/dose BID, respectively) resulted in a toxicity profile consistent with long-term exposure to corticosteroids, including adrenal atrophy and histopathological changes in several organ systems indicative of severe immune suppression. A no observable adverse effect level (NOAEL) could not be determined in this study. Although the clinical relevance of the findings in animals to humans is not clear, sustained glucocorticoid-related immune suppression may increase the risk of infection and possibly the risk for carcinogenesis.

Desoximetasone revealed no evidence of mutagenic or clastogenic potential based on the results of two in vitrogenotoxicity tests (Ames assay and Chinese hamster ovary cell chromosome aberration assay) and one in vivogenotoxicity test (mouse bone marrow micronucleus assay).

No evidence of impairment of male or female fertility was observed at subcutaneous desoximetasone doses up to 0.1 mg/kg/day (0.6 mg/m^2/day) in Sprague-Dawley rats.

14 CLINICAL STUDIES

Two multi-center, randomized, double-blind, vehicle-controlled clinical trials were conducted in 239 subjects aged 18 years and older with moderate to severe plaque psoriasis of the body. In both trials, randomized subjects applied Topicort Topical Spray or vehicle spray to the affected areas twice daily for 4 weeks. Enrolled subjects had a minimum body surface area of involvement of 10%, and a Physician's Global Assessment score (PGA) of 3 (moderate) or 4 (severe).

Efficacy was assessed at Week 4 as the proportion of subjects who were considered a Clinical Success ("clear" (0) or "almost clear" (1) according to the PGA scale). Table 2 presents the efficacy results.

Table 2. Number of Subjects (%) with Clinical Success (scored as clear or almost clear) at Week 4.
Parameter | Trial 1 |  | Trial 2
Parameter | Topicort N=59 | Vehicle N=60 | Topicort N=60 | Vehicle N=60
Clinical Success | 18 (30.5%) | 3 (5.0%) | 32 (53.3%) | 11 (18.3%)

16 HOW SUPPLIED/STORAGE AND HANDLING

16.1 How Supplied/Storage

Topicort®(desoximetasone) Topical Spray, 0.25% is a clear colorless liquid supplied in white, opaque bottles with white, opaque screw caps in the following sizes:

- 30 mL (NDC 51672-5281-3)
- 50 mL (NDC 51672-5281-4)
- 100 mL (2- 50mL bottles) (NDC 51672-5281-6)
- 100 mL (NDC 51672-5281-7)

STORAGE AND HANDLING

Store at controlled room temperature between 20°C to 25°C (68°F to 77°F), excursions permitted to 15°C to 30°C (59°F to 86°F). [See USP Controlled Room Temperature] Spray is flammable; avoid heat, flame or smoking when using this product.

Each unit is co-packaged with a manual spray pump for installation by the pharmacist.

16.2 Instructions for the Pharmacist

1. Remove the spray pump from the wrapper
2. Remove and discard the cap from the bottle
3. Keeping the bottle vertical, insert the spray pump into the bottle and turn clockwise until well-fastened
4. Dispense the bottle with the spray pump inserted
5. Label the bottle with "discard the product 30 days after dispensing"

17 PATIENT COUNSELING INFORMATION

See FDA-approved patient labeling (Patient Informationand Instructions for Use)

Inform patients of the following:

- Use this medication as directed by the physician. Do not use this medication for any disorder other than that for which it was prescribed.
- Topicort Topical Spray is for external use only.
- Avoid contact with eyes and use on the face, axilla or groin.
- To minimize the risk of adverse reactions:
  - do not bandage or otherwise cover or wrap the treated skin so as to be occlusive.
  - discontinue therapy when control is achieved. If no improvement is seen within 4 weeks, contact the physician.
  - do not use other corticosteroid-containing products with Topicort Topical Spray without first consulting with the physician.
- Advise patients that Topicort Topical Spray may require periodic evaluation for HPA axis suppression. Topical corticosteroids may have other endocrine effects [see Warnings and Precautions (5.1)] .
- Advise women to use Topicort Topical Spray on the smallest area of skin and for the shortest duration possible while pregnant or breastfeeding. Advise breastfeeding women not to apply Topicort Topical Spray directly to the nipple and areola to avoid direct infant exposure [see Use in Specific Populations (8.1and 8.2)].
- Report any signs of local or systemic adverse reactions including any visual symptoms to the physician.
- This medication is flammable; avoid heat, flame, or smoking when applying this product.
- Discard this product 30 days after dispensed by pharmacist.

Mfd. by: Taro Pharmaceuticals Inc., Brampton, Ontario, Canada L6T 1C1
Dist. by: TaroPharma®a division of Taro Pharmaceuticals U.S.A., Inc., Hawthorne, NY 10532
Revised: September 2021
PK-6681-4 113

Instructions for Use
TOPICORT ® (Top-i-cort)
(desoximetasone) topical spray

Important information: Topicort Topical Spray is for use on skin (topical) only.Do not get Topicort Topical Spray near or in your mouth, eyes or vagina.

Read the Instructions for Use before you start using Topicort Topical Spray and each time you get a refill. There may be new information. This information does not take the place of talking with your doctor about your medical condition or your treatment.

Parts of Topicort Topical Spray bottle (See Figure A).

Figure A

How to apply Topicort Topical Spray:

Step 1:Remove the cap from the pump top.

Step 2:Hold the bottle in an upright position while pointing the opening of the pump top in the direction of the affected area. To spray, push down on the pump top. Apply Topicort Topical Spray to the affected area as instructed by your doctor. (See Figure B).

Figure B

Step 3:Spray only enough Topicort Topical Spray to cover the affected area, for example, the elbow (See Figure C). Rub in Topicort Topical Spray gently to the affected area.

Figure C

Repeat Steps 2 and 3 to apply Topicort Topical Spray to other affected areas as instructed by your doctor.

Step 4: After applying Topicort Topical Spray, place the cap back onto the pump top (See Figure D).

Figure D

How should I store Topicort Topical Spray?

- Store Topicort Topical Spray at room temperature between 68˚F to 77˚F (20˚C to 25˚C).
- Throw away (discard) unused Topicort Topical Spray 30 days after it has been opened.
- Topicort Topical Spray is flammable. Keep away from heat, flames or smoke.

Keep Topicort Topical Spray and all medicines out of the reach of children.

This Instructions for Use has been approved by the U.S. Food and Drug Administration.

Mfd by: Taro Pharmaceuticals Inc., Brampton, Ontario, Canada L6T 1C1
Dist. by: TaroPharma a division of Taro Pharmaceuticals U.S.A., Inc., Hawthorne, NY 10532

Topicort®and TaroPharma®are registered trademarks of Taro Pharmaceuticals U.S.A., Inc. and/or its affiliates.

Revised: September 2021
PK-7265-0 110

PATIENT INFORMATION
TOPICORT®(Top-i-cort)
(desoximetasone) topical spray

Important information: Topicort Topical Spray is for use on skin (topical) only. Do not get Topicort Topical Spray near or in your mouth, eyes or vagina.

What is Topicort Topical Spray?
Topicort Topical Spray is a prescription corticosteroid medicine used to treat plaque psoriasis of the body in people 18 years of age and older.
It is not known if Topicort Topical Spray is safe and effective in children under 18 years of age. Topicort Topical Spray is not recommended for use in children under 18 years of age.

Before you use Topicort Topical Spray, tell your doctor about all of your medical conditions, including if you:

- have had irritation or other skin reaction to a steroid medicine in the past.
- have a skin infection. You may need medicine to treat the skin infection before you use Topicort Topical Spray.
- have thinning of the skin (atrophy) at the treatment site
- have adrenal gland problems
- have diabetes
- liver problems
- are pregnant or plan to become pregnant. It is not known if Topicort Topical Spray will harm your unborn baby. Topicort Topical Spray may increase your chance of having a low birthweight baby. If you use Topicort Topical Spray during pregnancy, use Topicort Topical Spray on the smallest area of the skin and for the shortest time needed.
- are breastfeeding or plan to breastfeed. It is not known if Topicort Topical Spray passes into your breast milk. If you use Topicort Topical Spray and breastfeed, use Topicort Topical Spray on the smallest area of the skin and for the shortest time needed. Do not apply Topicort Topical spray directly to the nipple and areola to avoid contact with your baby.

Tell your doctor about all the medicines you takeincluding prescription and over-the-counter medicines, vitamins and herbal supplements. Especially tell your doctor if you take other corticosteroid medicines by mouth or use other products on your skin that contain corticosteroids. Do not use other products containing a corticosteroid medicine while using Topicort Topical Spray without talking to your doctor first.

What should I avoid while using Topicort Topical Spray?
Topicort Topical Spray is flammable. Avoid heat, flames or smoking while applying Topicort Topical Spray to your skin.

How should I use Topicort Topical Spray?
See the " Instructions for Use" for detailed information about the right way to apply Topicort Topical Spray.

- Use Topicort Topical Spray exactly as your doctor tells you to use it.
- Your doctor should tell you how much Topicort Topical Spray to use and where to use it.
- Apply Topicort Topical Spray to the affected skin areas 2 times a day and rub it in gently.
- Do not bandage, cover, or wrap the treated skin area, unless your doctor tells you to.
- Use Topicort Topical Spray for the shortest amount of time needed to treat your plaque psoriasis. Tell your doctor if your skin condition is not getting better after 4 weeks of using Topicort Topical Spray. You should not use Topicort Topical Spray for longer than 4 weeks.
- Do not use Topicort Topical Spray on your face, armpits or groin.
- Do not use Topicort Topical Spray if you have thinning of your skin (atrophy) at the treatment site.
- Wash your hands after applying Topicort Topical Spray.

What are the possible side effects of Topicort Topical Spray?
Topicort Topical Spray may cause serious side effects, including:

- Symptoms of a disorder where the adrenal gland does not make enough of certain hormones (adrenal insufficiency) during treatment or after stopping treatment with Topicort Topical Spray. Your doctor may do blood tests to check for adrenal gland problems.
- Cushing's syndrome, a condition that happens when your body is exposed to large amounts of the hormone cortisol. Your doctor may do tests to check for this.
- High blood sugar (hyperglycemia) or diabetes mellitus that has not been diagnosed can happen when treated with Topicort Topical Spray.Your doctor may do tests to check for this .
- Skin reactions at the treated skin site.Tell your doctor if you get any skin reactions or skin infections.
- Eye problems.Using Topicort Topical Spray may increase your chance of getting cataracts and glaucoma. Do not get Topicort Topical Spray in your eyes because it may cause eye irritation. Tell your doctor if you have blurred vision or other vision problems during treatment with Topicort Topical Spray.

The most common side effects of Topicort Topical Spray includedryness, irritation and itching of skin at the treated site.
These are not all of the possible side effects of Topicort Topical Spray.
Call your doctor for medical advice about side effects. You may report side effects to FDA at 1-800-FDA-1088

How should I store Topicort Topical Spray?

- Store Topicort Topical Spray at room temperature between 68˚F to 77˚F (20˚C to 25˚C).
- Throw away (discard) unused Topicort Topical Spray after 30 days.

Keep Topicort Topical Spray and all medicines out of the reach of children.

General information about the safe and effective use of Topicort Topical Spray.
Medicines are sometimes prescribed for purposes other than those listed in a Patient Information leaflet. Do not use Topicort Topical Spray for a condition for which it was not prescribed. Do not give Topicort Topical Spray to other people, even if they have the same symptoms you have. It may harm them. You can ask your pharmacist or doctor for information about Topicort Topical Spray that is written for health professionals.

What are the ingredients in Topicort Topical Spray?
Active ingredient:desoximetasone
Inactive ingredients:glyceryl oleate, isopropyl alcohol, isopropyl myristate, L-menthol, and mineral oil
Mfd. by: Taro Pharmaceuticals Inc., Brampton, Ontario, Canada L6T 1C1
Dist. by: TaroPharma a division of Taro Pharmaceuticals U.S.A., Inc., Hawthorne, NY 10532
PK-7265-0 110

This Patient Information has been approved by the U.S. Food and Drug Administration.
Revised: September 2021

PACKAGE LABEL

PRINCIPAL DISPLAY PANEL - 100 mL Bottle Carton

NDC 51672-5281-7
100 mL

Rx only

Topicort®
(desoximetasone)
Topical Spray, 0.25%

0.25%

SPRAY

For Topical Use Only
Not For Oral, Ophthalmic, or Intravaginal Use

TaroPharma®